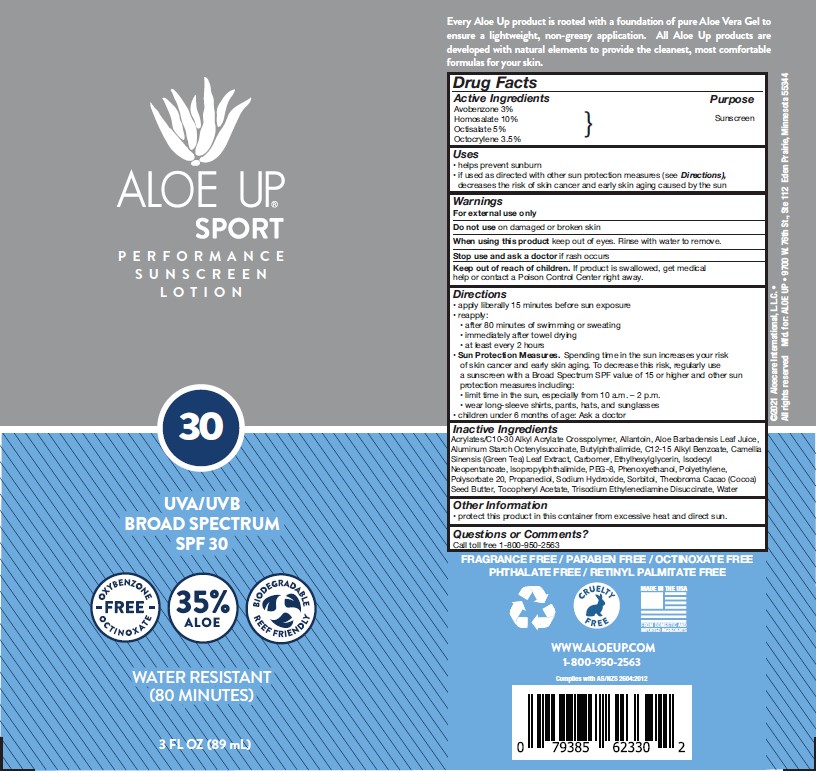 DRUG LABEL: CORETEX
NDC: 58443-0420 | Form: LOTION
Manufacturer: Prime Enterprises Inc.
Category: otc | Type: HUMAN OTC DRUG LABEL
Date: 20210910

ACTIVE INGREDIENTS: HOMOSALATE 73.5 mg/1 mL; OCTOCRYLENE 49 mg/1 mL; AVOBENZONE 29.4 mg/1 mL; OCTISALATE 49 mg/1 mL
INACTIVE INGREDIENTS: ETHYLHEXYLGLYCERIN; SORBITAN MONOOLEATE; CARBOMER HOMOPOLYMER, UNSPECIFIED TYPE; COCOA BUTTER; HIGH DENSITY POLYETHYLENE; PHENOXYETHANOL; CARBOMER INTERPOLYMER TYPE A (55000 CPS); ALKYL (C12-15) BENZOATE; POLYSORBATE 20; ALPHA-TOCOPHEROL ACETATE; WATER; ALOE VERA LEAF; SODIUM HYDROXIDE; EDETATE DISODIUM ANHYDROUS; HYPROMELLOSES; PROPYLENE GLYCOL

Fragrance Free Reef Friendly Sunscreen Lotion Broad Spectrum SPF 30

Active Ingredients

Avobenzone 3.0%

Octocrylene 3.5%

Homosalate 10%

Octisalate 5%

Purpose

Sunscreen

Uses

- helps prevent sunburn
  - if used as directed with other sun protection measures (see Directions) decreases the risk of skin cancer and early skin aging caused by the sun

Warnings

For external use only

Do not use on damaged or broken skin

When using this product keep out of eyes. Rinse with water to remove.

Stop use and ask a doctor if rash occurs

Keep out of reach of children. If product is swallowed, get medical help or contact a Poison Control Center right away.

Directions

- apply liberally 15 minutes before sun exposure
- reapply:
- after 80 minutes of swimming or sweating
- immediately after towel drying
- at least every 2 hours
- Sun Protection Measures Spending time in the sun increases your risk of skin cancer and early skin aging. To decrease this risk, regularly use a sunscreen with a broad spectrum SPF value of 15 or higher and other sun protection measures including:
- limit time in the sun, especially from 10 a.m. - 2 p.m.
- wear long-sleeve shirts, pants, hats, and sunglasses
- children under 6 months of age: Ask a doctor

INACTIVE INGREDIENTS

Acrylates/C10-30 Alkyl Acrylate Crosspolymer, Allantoin, Aloe Barbadensis Leaf Juice, Aluminum Starch Octenylsuccinate, Butylphthalimide, C12-15 Alkyl Benzoate, Camellia Sinensis (Green Tea) Leaf Extract, Carbomer, Ethylhexylglycerin, Isodecyl Neopentanoate, Isopropylphthalimide, PEG-8, Phenoxyethanol, Polyethylene, Polysorbate 20, Propanediol, Sodium Hydroxide, Sorbitol, Theobroma Cacao (Cocoa) Seed Butter, Tocopheryl Acetate, Trisodium Ethylenediamine Disuccinate, Water

Other Information

- protect this product in this container from excessive heat and direct sun.

Questions or Comments?

Call toll free 1-800-950-2563